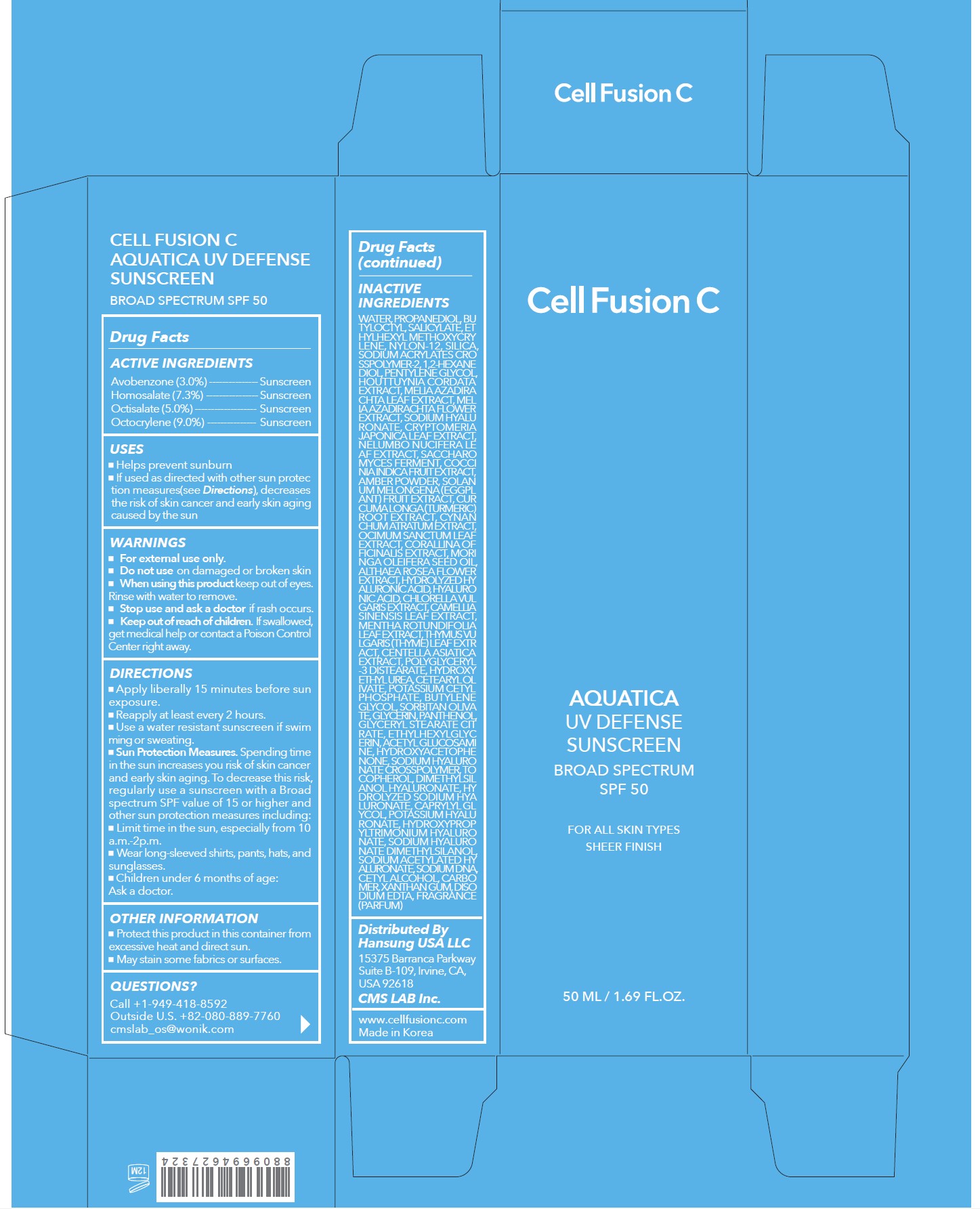 DRUG LABEL: Cell Fusion C Aquatica UV Defense Sunscreen Broad Spectrum SPF 50
NDC: 52554-9061 | Form: CREAM
Manufacturer: CMS LAB Inc.
Category: otc | Type: HUMAN OTC DRUG LABEL
Date: 20250212

ACTIVE INGREDIENTS: HOMOSALATE 7.3 g/50 mL; OCTOCRYLENE 9 g/50 mL; OCTISALATE 5 g/50 mL; AVOBENZONE 3 g/50 mL
INACTIVE INGREDIENTS: WATER

52554-9061-1 Cell Fusion C Aquatica UV Defense Sunscreen Broad Spectrum SPF 50 50mL

Drug Facts

ACTIVE INGREDIENTS

Avobenzone 3.0%
Homosalate 7.3%
Octisalate 5.0%
Octocrylene 9.0%

PURPOSE

Sunscreen

USES

- Helps prevent sunburn
- If used as directed with other sun protection measures (see Directions), decreases the risk of skin cancer and early skin aging caused by the sun

WARNINGS

For external use only

- Do not use on damaged or broken skin

- When using this product keep out of the eyes. Rinse with water to remove.

- Stop use and ask a doctor if rash occurs

- Keep out of reach of children. If swallowed, get medical help or contact a Poison Control Center right away.

DIRECTIONS

- Apply generously and evenly 15 minutes before sun exposure.
- Reapply at least every 2 hours.
- Use a water resistant sunscreen if swimming or sweating.
- Sun Protection Measures. Spending time in the sun increases your risk of skin cancer and early skin aging. To decrease this risk, regularly use a sunscreen with a Broad Spectrum SPF value of 15 or higher and other sun protection measures including:

- Limit time in the sun, especially from 10 a.m.-2 p.m.
- Wear long-sleeved shirts, pants, hats, and sunglasses
- Children under 6 months of age: Ask a doctor.

OTHER INFORMATION

- Protect this product in this container from excessive heat and direct sun.
- May stain some fabrics or surfaces.

INACTIVE INGREDIENTS

Water, Propanediol, Butyloctyl, Salicylate, Ethylhexyl Methoxycrylene, Nylon-12, Silica, Sodium Acrylates Crosspolymer-2, 1,2-Hexanediol, Pentylene Glycol, Houttuynia Cordata Extract, Melia Azadirachta Leaf Extract, Melia Azadirachta Flower Extract, Sodium Hyaluronate, Cryptomeria Japonica Leaf Extract, Nelumbo Nucifera Leaf Extract, Saccharomyces Ferment, Coccinia Indica Fruit Extract, Amber Powder, Solanum Melongena (Eggplant) Fruit Extract, Curcuma Longa (Turmeric) Root Extract, Cynanchum Atratum Extract, Ocimum Sanctum Leaf Extract, Corallina Officinalis Extract, Moringa Oleifera Seed Oil, Althaea Rosea Flower Extract, Hydrolyzed Hyaluronic Acid, Hyaluronic Acid, Chlorella Vulgaris Extract, Camellia Sinensis Leaf Extract, Mentha Rotundifolia Leaf Extract, Thymus Vulgaris (Thyme) Leaf Extract, Centella Asiatica Extract, Polyglyceryl-3 Distearate, Hydroxyethyl Urea, Cetearyl Olivate, Potassium Cetyl Phosphate, Butylene Glycol, Sorbitan Olivate, Glycerin, Panthenol, Glyceryl Stearate Citrate, Ethylhexylglycerin, Acetyl Glucosamine, Hydroxyacetophenone, Sodium Hyaluronate Crosspolymer, Tocopherol, Dimethylsilanol Hyaluronate, Hydrolyzed Sodium Hyaluronate, Caprylyl Glycol, Potassium Hyaluronate, Hydroxypropyltrimonium Hyaluronate, Sodium Hyaluronate Dimethylsilanol, Sodium Acetylated Hyaluronate, Sodium DNA, Cetyl Alcohol, Carbomer, Xanthan Gum, Disodium EDTA, Fragrance (Parfum)

QUESTIONS?

Call +1-949-418-8592
Outside U.S. +82-080-889-7760
cmslab_os@wonik.com

Distributed By
Hansung USA LLC
15375 Barranca Parkway
Suite B-109, Irvine, CA USA 92618
CMS LAB Inc.
www.cellfusionc.com
Made in Korea

PRINCIPAL DISPLAY PANEL: 50 ML / 1.69 FL.OZ. Carton

Cell Fusion C

AQUATICA
UV DEFENSE
SUNSCREEN
BROAD SPECTRUM
SPF 50
FOR ALL SKIN TYPES
SHEER FINISH
50 ML / 1.69 FL.OZ.